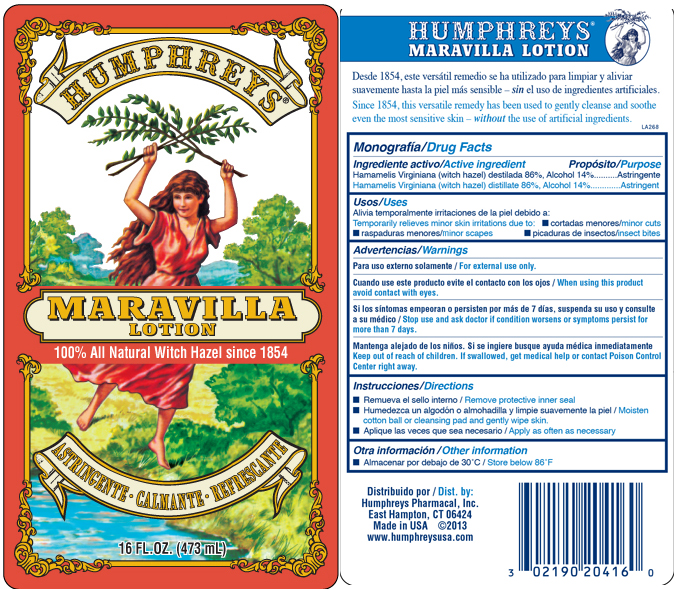 DRUG LABEL: Humphreys Maravilla
NDC: 0219-0204 | Form: LIQUID
Manufacturer: Humphreys Pharmacal, Incorporated
Category: otc | Type: HUMAN OTC DRUG LABEL
Date: 20241206

ACTIVE INGREDIENTS: WITCH HAZEL 1 g/1 mL

Monografía/Drug Facts

ACTIVE INGREDIENT

Hamamelis Virginiana (witch hazel) destilada 86%, Alcohol 14%
Hamamelis Virginiana (witch hazel) distillate 86%, Alcohol 14%

Propósito/Purpose

Astringente
Astringent

Usos/Uses:

Alivia temporalmente irritaciones de la piel debido a:

- cortadas menores
- raspaduras menores
- picaduras de insectos

Temporarily relieves minor skin irritations due to:

- minor cuts
- minor scrapes
- insect bites

Advertencias / Warnings:

Para uso externo solamente / For external use only.
Cuando use este producto evite el contacto con los ojos / When using this product avoid contact with eyes.

STOP USE

Si los síntomas empeoran o persisten por más de 7 días, suspenda su uso y consulte a su médico / Stop use and ask doctor if condition worsens or symptoms persist for more than 7 days.

KEEP OUT OF REACH OF CHILDREN

Mantenga alejado de los niños. Si se ingiere busque ayuda médica inmediatamente
Keep out of reach of children. If swallowed, get medical help or contact Poison Control Center right away.

Instrucciones/Directions:

- Remueva el sello interno / Remove protective inner seal
- Humedezca un algodón o almohadilla y limpie suavemente la piel / Moisten cotton ball or cleansing pad and gently wipe skin.
- Aplique las veces que sea necesario / Apply as often as necessary

Otra información / Other information

Almacenar por debajo de 30C / Store below 86F

QUESTIONS

Distribuido por / Dist. by:
Humphreys Pharmacal, Inc.
East Hampton, CT 06424
Made in USA

www.humphreysusa.com

Product Packaging

The labels shown below represent a sample of that currently in use. Additional packaging may also be available.
HUMPHREYS
MARAVILLA
LOTION
100% All Natural Witch Hazel since 1854
ASTRINGENTE - CALMANTE - REFRESCANTE